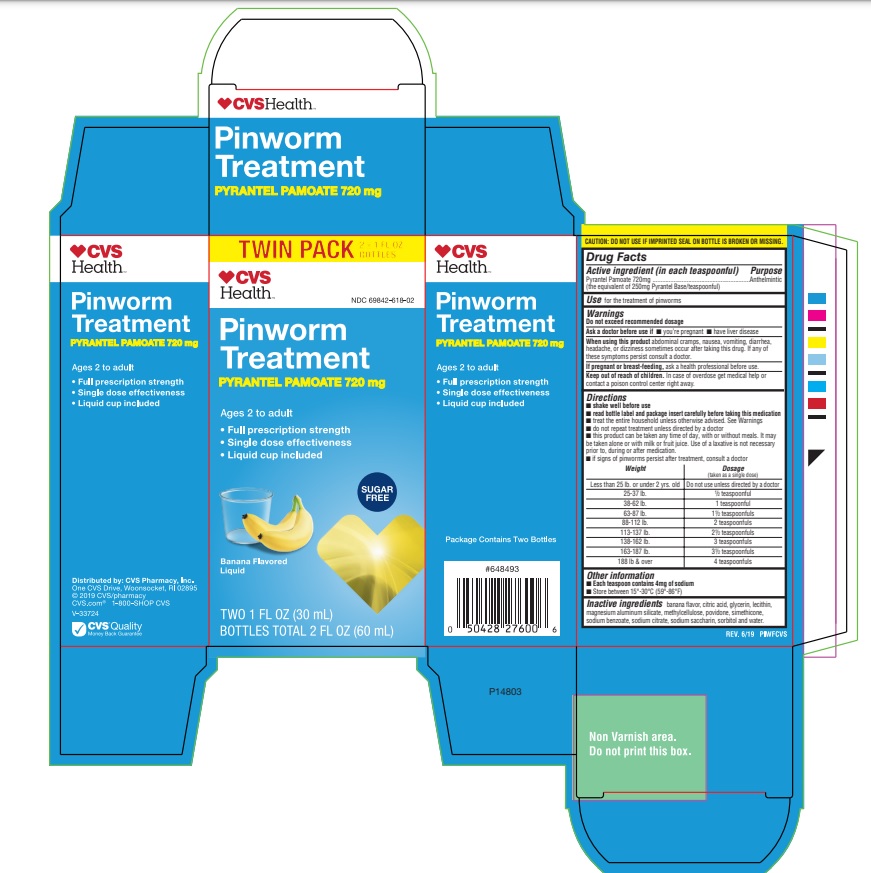 DRUG LABEL: CVS Pinworm Treatment
NDC: 69842-618 | Form: SUSPENSION
Manufacturer: CVS PHARMACY INC
Category: otc | Type: HUMAN OTC DRUG LABEL
Date: 20241218

ACTIVE INGREDIENTS: PYRANTEL PAMOATE 144 mg/1 mL
INACTIVE INGREDIENTS: CITRIC ACID MONOHYDRATE; GLYCERIN; LECITHIN, SOYBEAN; MAGNESIUM ALUMINUM SILICATE; METHYLCELLULOSE (100 CPS); POVIDONE; DIMETHICONE; SODIUM BENZOATE; SODIUM CITRATE; SACCHARIN SODIUM; SORBITOL; WATER

Drug Facts

Active ingredient (in each mL)

Pyrantel Pamoate 144mg/mL (the equivalent of 50mg pyrantel base)

Purpose

Anthelimintic

INDICATIONS AND USAGE

Uses for the treatment of pinworns

Warnings Do not exceed recommended dosage

Ask a doctor before use if

- you're pregnant
- have liver disease

When using this product abdominal cramps, nausea, vomiting, diarrhea, headache, or dizziness sometimes occur after taking this drug. If any of these symptoms persist, consult a doctor.

Keep out of reach of children. In case of overdose get medical help or contact a poison control center right away.

Directions

- shake well before use
- read bottle label and package insert carefully before taking this medication
- treat the entire household unless otherwise advised
- do not repeat treatment unless directed by a doctor
- this product can be taken any time of day, with or without meals. It may be taken alone or with milk or fruit juice. Use of a laxative is not necessary prior to, during or after medication
- it signs of pinworms persist after treatment, consult a doctor

Weight | Dosage (taken as a single dose)
Less than 25 lb. or under 2 yrs.old | Do not use unless directed by a doctor
25-37 lb. | 1/2 teaspoonful
38-62 lb. | 1 teaspoonful
63-87 lb. | 1 1/2 teaspoonfuls
88-112 lb. | 2 teaspoonfuls
113-137 lb. | 2 1/2 teaspoonfuls
138-162 lb. | 3 teaspoonfuls
163-187 lb. | 3 1/2 teaspoonfuls
188 lb. and over | 4 teaspoonfuls

Inactive ingredients

banana flavor, citric acid, gylcerin, lecithin, magnesium aluminum silicate, methylcellulose, povidone, simethicone, sodium benzoate, sodium citrate, sodium saccharin, sorbitol, and water